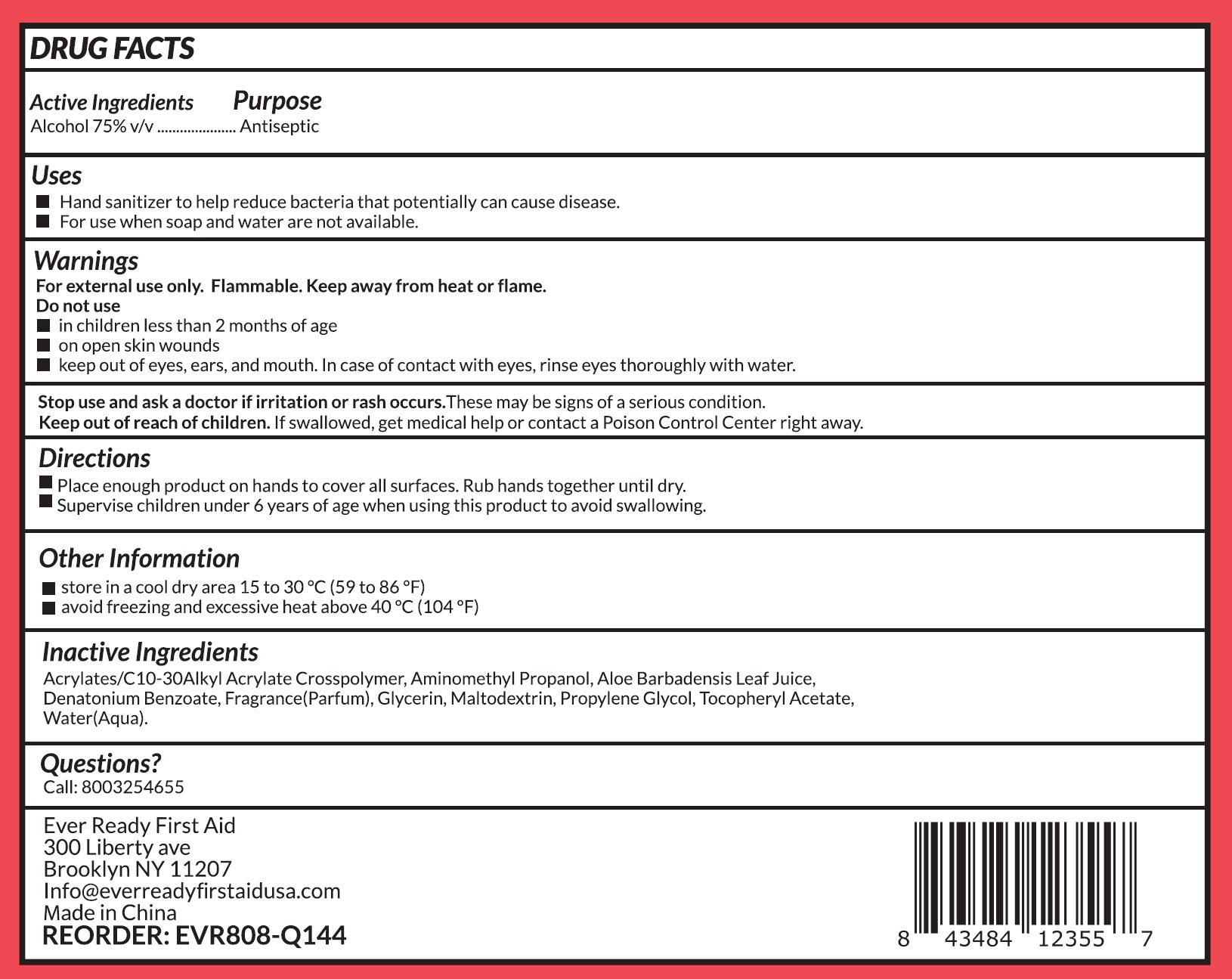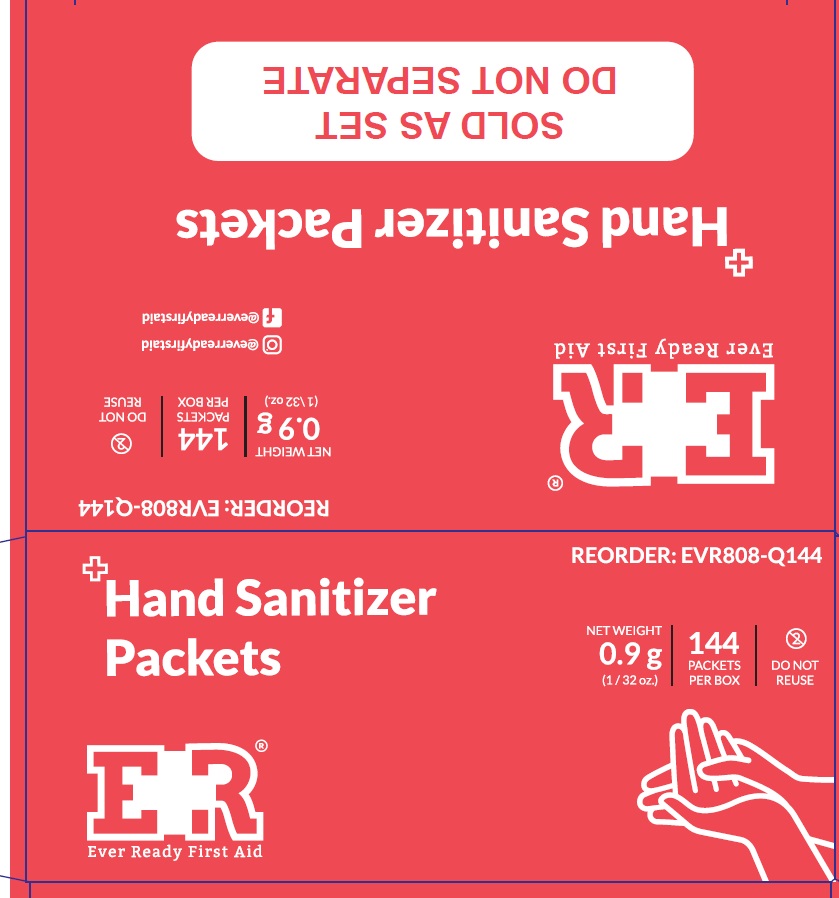 DRUG LABEL: ER Hand Sanitizer Packets
NDC: 72976-016 | Form: GEL
Manufacturer: EVER READY FIRST AID
Category: otc | Type: HUMAN OTC DRUG LABEL
Date: 20240111

ACTIVE INGREDIENTS: ALCOHOL 75 mL/100 mL
INACTIVE INGREDIENTS: WATER; GLYCERIN; PROPYLENE GLYCOL; ACRYLATES/C10-30 ALKYL ACRYLATE CROSSPOLYMER (60000 MPA.S); TOCOPHERYL GLUCOSIDE; AMINOMETHYLPROPANOL; DENATONIUM BENZOATE; MALTODEXTRIN; ALOE

Active ingredient

Alcohol, 75% v/v

Purpose Antiseptic

Uses

- Hand sanitizer to help reduce bacteria that potentially can cause disease
- For use when soap and water are not available

Warnings

For external use only.

Flammable, keep away from heat or flame.

Do not use

- In children less than 2 months of age
- On open skin wounds
- Keep out of eyes, ears, and mouth. In case of contact with eyes, rinse eyes thoroughly with water.

Stop use and ask a doctor if irritation or rash occurs.These may be signs of a serious condition

Keep out of reach of children. If swallowed, get medical help or contact a Poison Control Center right away

Directions

Place enough products on hands to cover all surfaces. Rub hands together until dry

Supervise children under 6 years of age when using this product to avoid swallowing

Other information

Store in a cool dry area 15 to 30C (59 to 86F)

Avoid freezing and excessive heat above 40V (104F)

Inactive ingredients

Acrylates/ C10-C30 alkyl acrylate crossploymer, Aminomethyl propanol, Aloe barbadensis leaf jiuce, Denatonium benzoate, Fragrance, Glycerin, Maltodextrin, Propylene glycol, Tocopheryl acetate, Water